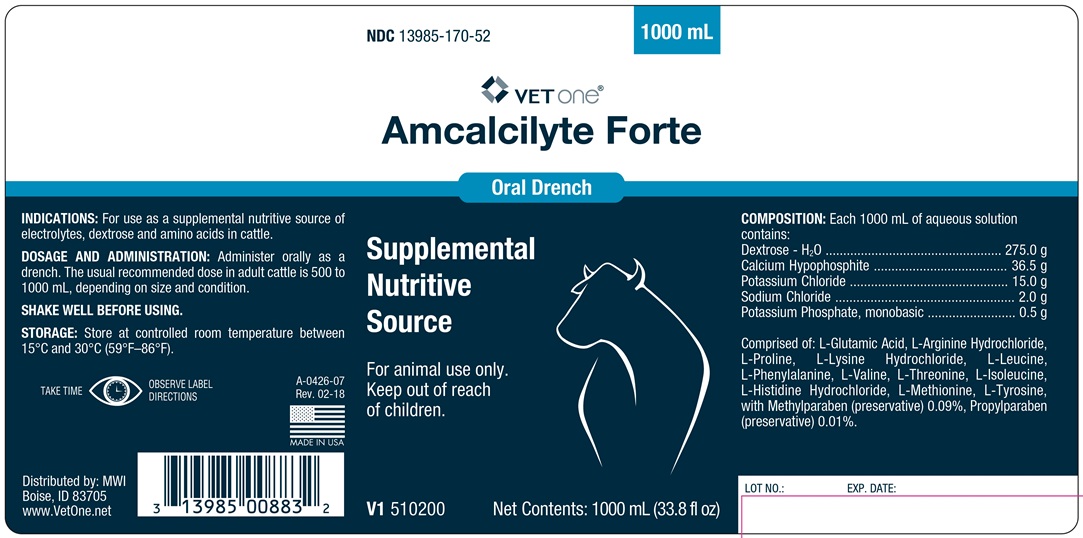 DRUG LABEL: AMCALCILYTE 
NDC: 13985-170 | Form: SOLUTION
Manufacturer: MWI Veterinary Supply, Inc.
Category: animal | Type: OTC ANIMAL DRUG LABEL
Date: 20180418

ACTIVE INGREDIENTS: CALCIUM HYPOPHOSPHITE 36.5 g/1000 mL; DEXTROSE MONOHYDRATE 275 g/1000 mL; POTASSIUM CHLORIDE 15 g/1000 mL; POTASSIUM PHOSPHATE, MONOBASIC 0.5 g/1000 mL; SODIUM CHLORIDE 2 g/1000 mL

Amcalcilyte Forte

INDICATIONS AND USAGE

Oral Drench

Supplemental Nutritive Source

For Animal Use Only

Keep out of reach of children

INDICATIONS

For use as a supplemental nutritive source of electrolytes, dextrose and amino acids in cattle.

DOSAGE AND ADMINISTRATION

Administer orally as a drench. The usual recommended dose in adult cattle is 500 to 1000 mL, depending on size and condition.

SHAKE WELL BEFORE USING.

STORAGE

Store at controlled room temperature between 15° and 30°C (59°-86°F)

TAKE TIME OBSERVE LABEL DIRECTIONS

COMPOSITION

Each 1000 mL of aqueous solution contains:

Dextrose • H2O ....................................... 275.0 g
Calcium Hypophosphite ............................ 36.5 g
Potassium Chloride .................................. 15.0 g
Sodium Chloride ........................................ 2.0 g
Potassium Phosphate, monobasic ............... 0.5 g

Comprised of: L-Glutamic Acid, L-Arginine Hydrochloride, L-Proline, L-Lysine Hydrochloride, L-Leuicne, L-Phenylalanine, L-Valine, L-Threonine, L-Isoleucine, L-Histidine Hydrochloride, L-Metionine, L-Tyrosine, with Methylparaben (preservative) 0.09%, Propylparaben (preservative)0.01%